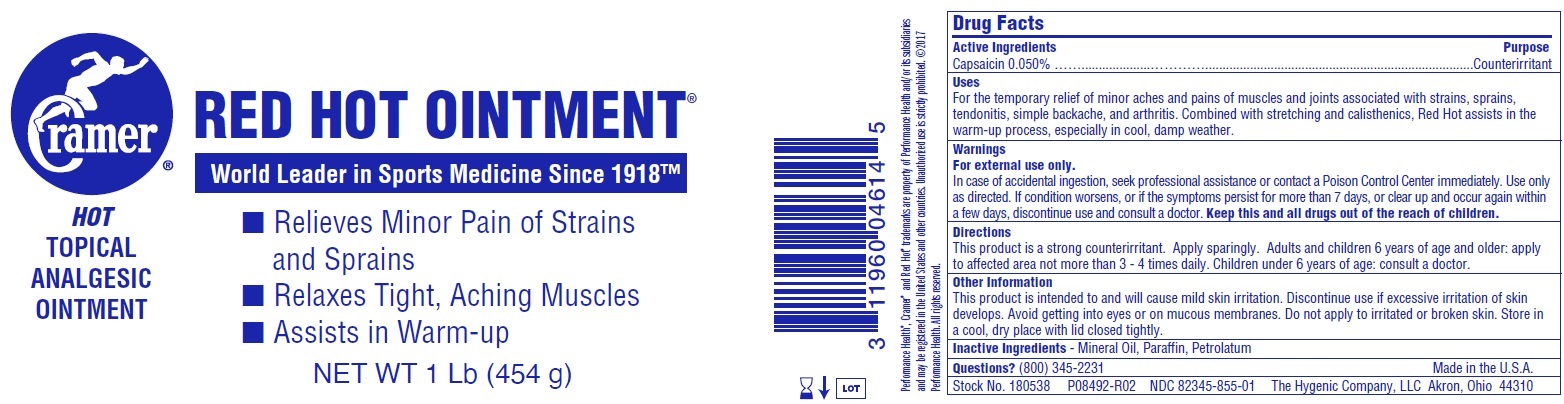 DRUG LABEL: Red hot
NDC: 82345-855 | Form: OINTMENT
Manufacturer: The Hygenic Company, LLC
Category: otc | Type: HUMAN OTC DRUG LABEL
Date: 20231025

ACTIVE INGREDIENTS: CAPSAICIN 0.5 mg/1 g
INACTIVE INGREDIENTS: MINERAL OIL; PARAFFIN; PETROLATUM

Red hot ointment

Active Ingredients

Methyl Salicylate 12.5%

Capsaicin 0.025%

Purpose

Counterirritant

Uses

For the temporary relief of minor aches and pains of muscles and joints associated with strains, sprains, tendonitis, simple backache, and arthritis. Combined with stretching and calisthenics, Red Hot assists in the warm-up process, especially in cool, damp weather.

Warnings

In case of accidental ingestion, seek professional assistance or contact a Poison Control Center immediately. Use only as directed. If condition worsens, or if the symptoms persist for more than 7 days, or clear up and occur again within a few days, discontinue use and consult a doctor. For external use only.

Directions

This product is a strong counterirritant. Apply sparingly. Adults and children 6 years of age and older: apply to affected area not more than 3 - 4 times daily. Children under 6 years of age: consult a doctor.

Other Information

This product is intended to and will cause mild skin irritation. Discontinue use if excessive irritation of skin develops. Avoid getting into eyes or on mucous membranes. Do not apply to irritated or broken skin. Store in a cool, dry place with lid closed tightly.

Inactive Ingredients

Mineral Oil, Paraffin, Petrolatum

Questions?

(800) 345-2231